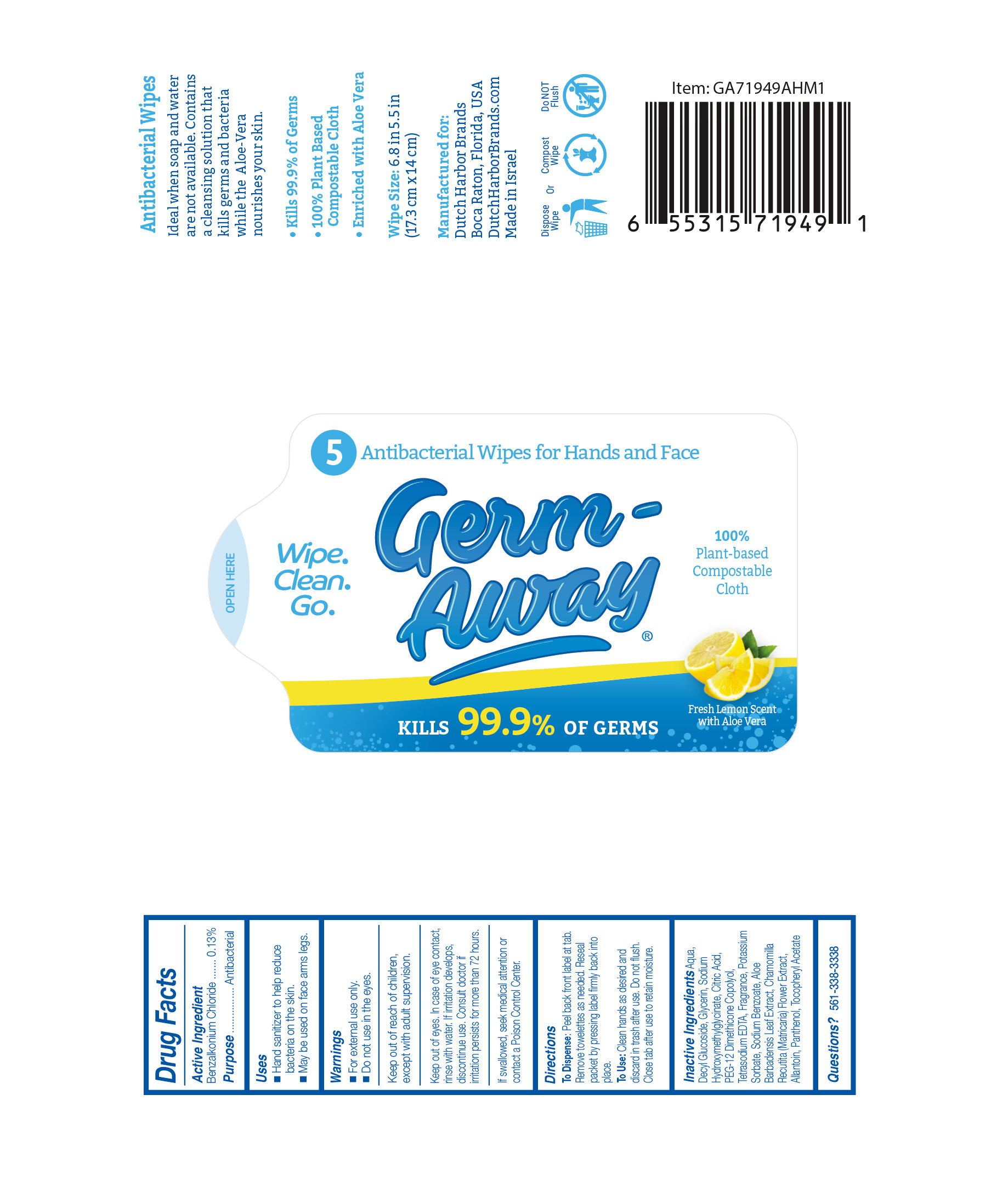 DRUG LABEL: Germ Away
NDC: 74680-101 | Form: CLOTH
Manufacturer: Unico International Trading Corp
Category: otc | Type: HUMAN OTC DRUG LABEL
Date: 20200528

ACTIVE INGREDIENTS: BENZALKONIUM CHLORIDE 0.001 1/1 1
INACTIVE INGREDIENTS: GLYCERIN; PANTHENOL; WATER; PEG-12 DIMETHICONE (300 CST); ALPHA-TOCOPHEROL ACETATE; SODIUM HYDROXYMETHYLGLYCINATE; CHAMOMILE; DECYL GLUCOSIDE; SODIUM BENZOATE; ALOE VERA LEAF; POTASSIUM SORBATE; EDETATE SODIUM; ALLANTOIN; ANHYDROUS CITRIC ACID

Germ Away

Active ingredient

Benzalkonium Chloride 0.1%

Keep out of the reach of children.

Keep out of reach of children, except with adult supervision.

Warnings

For external use only. Do not use in the eyes.

Keep out of eyes. In case of eye contact, rinse with water. If irritation develops, discontinue use. Consult doctor if irritation persists for more than 72 hours.

If swallowed, seek medical attention or contact a Poison Control Center.

To use

For external use only. Do not use in the eyes.

Keep out of eyes. In case of eye contact, rinse with water. If irritation develops, discontinue use. Consult doctor if irritation persists for more than 72 hours.

If swallowed, seek medical attention or contact a Poison Control Center.

Inactive Ingredients

Aqua, Decyl Glucoside, Glycerin, Sodium Hydroxymethylglycinate, Citric Acid, PEG-12 Dimethicone Copolyol, Tetrasodium EDTA, Potassium Sorbate, Sodium Benzoate, Aloe Barbadensis Leaf Extract, Chamomilla Recutita (Matricaria) Flower Extract, Allantoin, Panthenol, Tocopheryl Acetate

Purpose

Anti-bacterial

To dispense

Peel back from label at tab. Remove towelettes as needed. Reseal packet by pressing label firmly back into place.